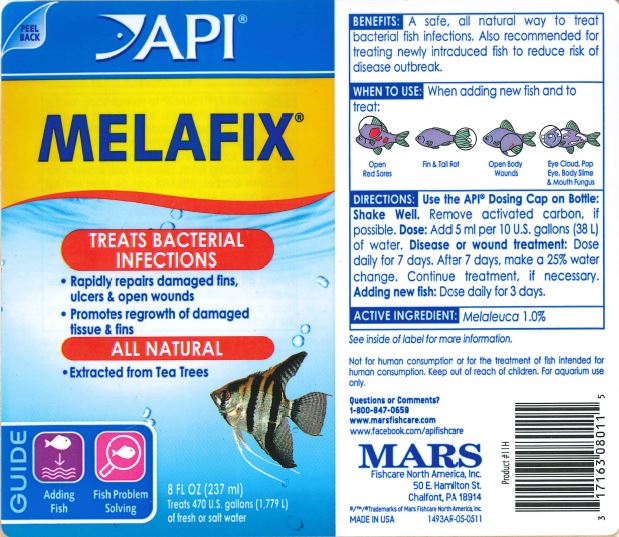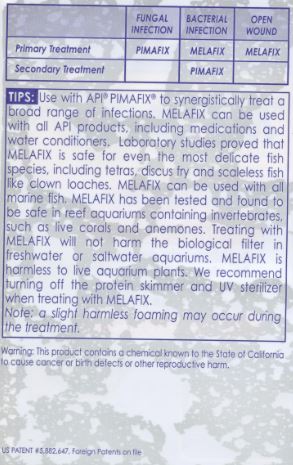 DRUG LABEL: API MELAFIX
NDC: 17163-011 | Form: LIQUID
Manufacturer: MARS FISHCARE NORTH AMERICA, INC.
Category: animal | Type: OTC ANIMAL DRUG LABEL
Date: 20191219

ACTIVE INGREDIENTS: CAJUPUT OIL 1 g/100 mL

Drug Label

INDICATIONS AND USAGE

WHEN TO USE:

When adding new fish and to treat:

Open Red Sores

Fin and Tail Rot

Open Body Wounds

Eye Cloud, Pop Eye, Body Slime and Mouth Fungus

DIRECTIONS:

Use the API Dosing Cap on Bottle:

Shake well. Remove activated carbon, if possible.

Dose:

Add 5 ml per 10 U.S. gallons (38 L) of water.

Disease or wound treatment:

Dose daily for 7 days. After 7 days, make a 25% water change. Continue treatment, if necessary.

Adding new fish:

Dose daily for 3 days.

ACTIVE INGREDIENT: Melaleuca 1.0%

See inside of label for more information.

USER SAFETY WARNINGS

FUNGAL INFECTION BACTERIAL INFECTION OPEN WOUND

Primary Treatment PIMAFIX MELAFIX MELAFIX

Secondary Treatment PIMAFIX

TIPS:

Use with API PIMAFIX to synergistically treat a broad range of infections. MELAFIX can be used with all API products, including medications and water conditioners. Laboratory studies proved that MELAFIX is safe for even the most delicate fish species, including tetras, discus fry and scaleless fish like clown loaches. MELAFIX can be used with all marine fish. MELAFIX has been tested and found to be safe in reef aquariums containing invertebrates, such as live corals and anemones. Treating with MELAFIX will not harm the biological filter in freshwater or saltwater aquariums. MELAFIX is harmless to live aquarium plants. We recommend turning off the protein skimmer and UV sterilizer when treating with MELAFIX.

Note: a slight harmless foaming may occur during the treatment.

Warning:

This product contains a chemical known by the State of California to cause cancer or birth defects or other reproductive harm.

Not for human consumption or for the treatment of fish intended for human consumption. Keep out of reach of children. For aquarium use only.

Questions or Comments?

1-800-847-0659

www.marsfishcare.com

www.facebook.com/apifishcare

PACKAGE LABEL

API

MELAFIX

TREATS BACTERIAL

INFECTIONS

Rapidly repairs damaged fins,

ulcers and open wounds

Promotes regrowth of damaged tissue and fins

ALL NATURAL

Extracted from Tea Trees

GUIDE

Adding Fish

Fish Problem Solving

8 FL OZ (237 ml)

Treats 470 U.s. gallons (1,779 L)

of fresh or salt water